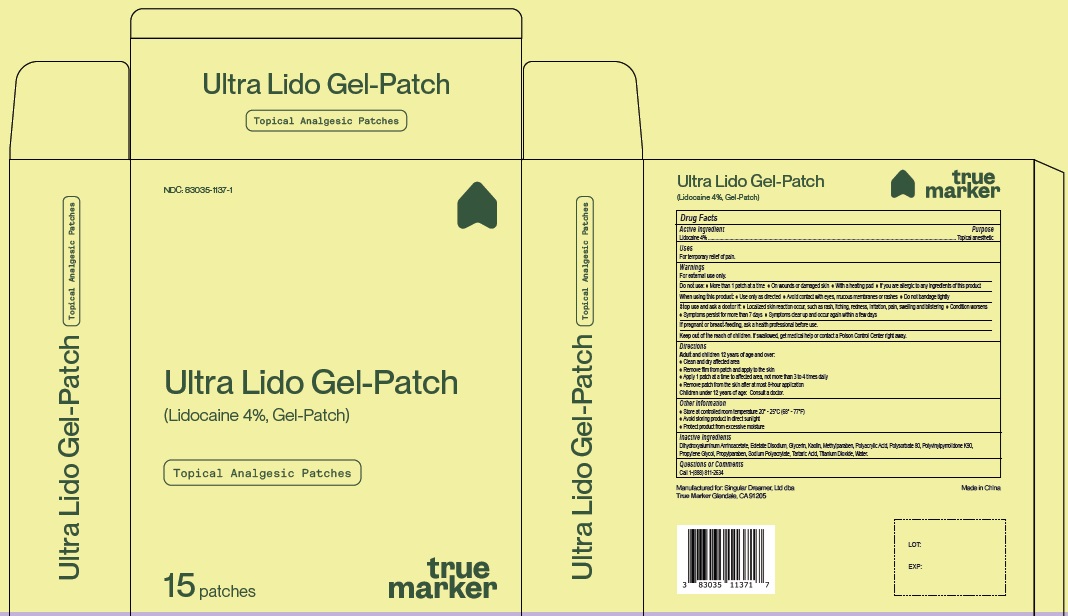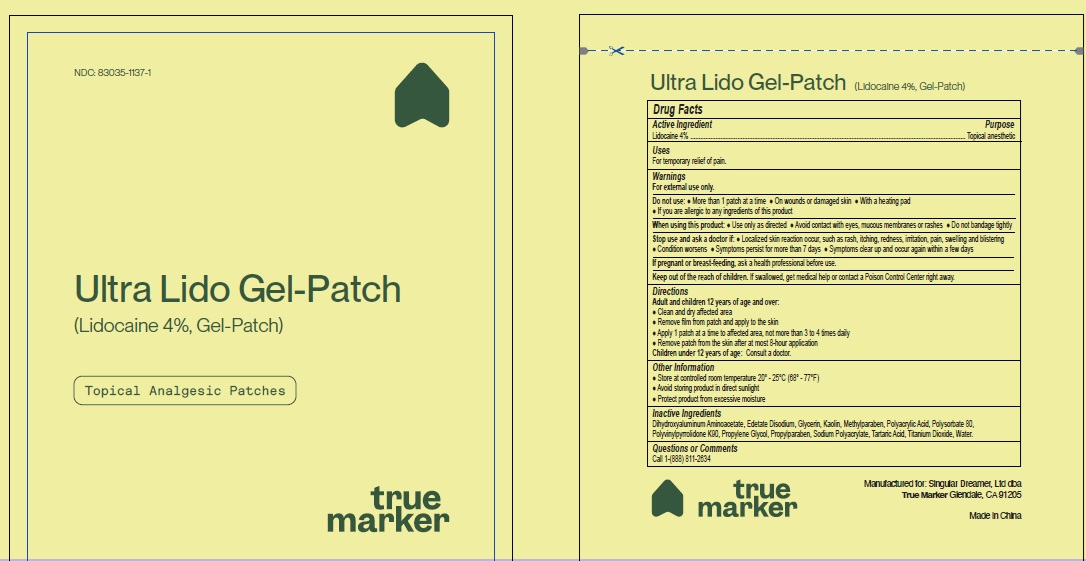 DRUG LABEL: Ultra Lido Gel Patch
NDC: 83035-1137 | Form: PATCH
Manufacturer: Singular Dreamer, Ltd dba True Marker
Category: otc | Type: HUMAN OTC DRUG LABEL
Date: 20240722

ACTIVE INGREDIENTS: LIDOCAINE 4 g/100 g
INACTIVE INGREDIENTS: DIHYDROXYALUMINUM AMINOACETATE; EDETATE DISODIUM; GLYCERIN; KAOLIN; METHYLPARABEN; POLYACRYLIC ACID (250000 MW); POLYSORBATE 80; POVIDONE K90; PROPYLENE GLYCOL; PROPYLPARABEN; SODIUM POLYACRYLATE (2500000 MW); TARTARIC ACID; TITANIUM DIOXIDE; WATER

Active Ingredient Purposes

Lidocaine 4.00% .....................................................Topical anesthetic

Uses

For temporary relief of pain.

Warnings

- For External Use only

- Do not use: ● More than 1 patch at a time ● On wounds or damaged skin ● With a heating pad ● If you are allergic to any ingredients of this product

When using this product:

- Use only as directed ● Avoid contact with eyes, mucous membranes or rashes ● Do not bandage tightly

Stop use and ask a doctor if:

- Localized skin reaction occur, such as rash, itching, redness, irritation, pain, swelling and blistering ● Condition worsens
  ● Symptoms persist for more than 7 days ● Symptoms clear up and occur again within a few days

- If pregnant or breast-feeding, ask a health professional before use.

- Keep out of the reach of children. If swallowed, get medical help or contact a Poison Control Center right away.

Directions

Adult and children 12 years of age and over:

- Clean and dry affected area
- Remove film from patch and apply to the skin
- Apply 1 patch at a time to affected area, not more than 3 to 4 times daily
- Remove patch from the skin after at most 8-hour application

Children under 12 years of age: Consult a doctor.

Other Information

● Store at controlled room temperature 20° - 25°C (68° - 77°F)
● Avoid storing product in direct sunlight
● Protect product from excessive moisture

Inactive Ingredients

Aloe Barbadensis Leaf (Aloe Vera Gel) Juice, Aqua (Deionized Water),Carbomer, Cetearyl Alcohol, Ethylhexylglycerin, Glycol Stearate,
Glyceryl Stearate, Helianthus Annuus (Sunflower) Oil,Phenoxyethanol,Polysorbate-60, Simmondsia Chinensis (Jojoba) Oil, Stearic Acid,
Triethanolamine.

Questions or Comments
Call 1-(888) 811-2634